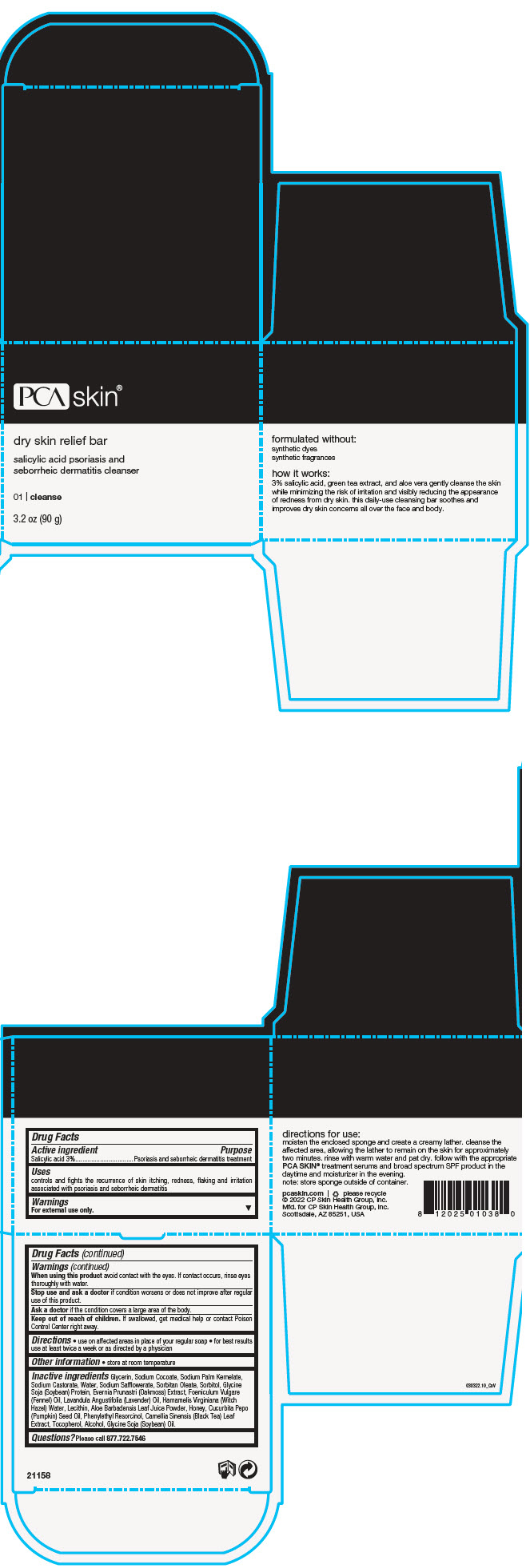 DRUG LABEL: Dry Skin Relief Bar
NDC: 68726-800 | Form: SOAP
Manufacturer: CP Skin Health Group, Inc.
Category: otc | Type: HUMAN OTC DRUG LABEL
Date: 20241209

ACTIVE INGREDIENTS: SALICYLIC ACID 3 g/100 g
INACTIVE INGREDIENTS: GLYCERIN; SODIUM COCOATE; SODIUM PALM KERNELATE; SODIUM CASTORATE; WATER; SODIUM SAFFLOWERATE; SORBITAN MONOOLEATE; SORBITOL; SODIUM HYDROXIDE; FENNEL OIL; SOYBEAN LECITHIN; LAVENDER OIL; HAMAMELIS VIRGINIANA TOP WATER; ALOE VERA LEAF; TEA LEAF; PUMPKIN SEED OIL; HONEY; PHENYLETHYL RESORCINOL; SOY PROTEIN; ALCOHOL; TOCOPHEROL; EVERNIA PRUNASTRI; SOYBEAN OIL

Dry Skin Relief Bar

Drug Facts

Active ingredient

Salicylic acid 3%

Purpose

Psoriasis and seborrheic dermatitis treatment

Uses

controls and fights the recurrence of skin itching, redness, flaking and irritation associated with psoriasis and seborrheic dermatitis

Warnings

For external use only.

When using this product avoid contact with the eyes. If contact occurs, rinse eyes thoroughly with water.

Stop use and ask a doctor if condition worsens or does not improve after regular use of this product.

Ask a doctor if the condition covers a large area of the body.

Keep out of reach of children. If swallowed, get medical help or contact Poison Control Center right away.

Directions

- use on affected areas in place of your regular soap
- for best results use at least twice a week or as directed by a physician

Other information

- store at room temperature

Inactive ingredients

Glycerin, Sodium Cocoate, Sodium Palm Kernelate, Sodium Castorate, Water, Sodium Safflowerate, Sorbitan Oleate, Sorbitol, Glycine Soja (Soybean) Protein, Evernia Prunastri (Oakmoss) Extract, Foeniculum Vulgare (Fennel) Oil, Lavandula Angustifolia (Lavender) Oil, Hamamelis Virginiana (Witch Hazel) Water, Lecithin, Aloe Barbadensis Leaf Juice Powder, Honey, Cucurbita Pepo (Pumpkin) Seed Oil, Phenylethyl Resorcinol, Camellia Sinensis (Black Tea) Leaf Extract, Tocopherol, Alcohol, Glycine Soja (Soybean) Oil.

Questions?

Please call 877.722.7546

PRINCIPAL DISPLAY PANEL - 90 g Jar Box

PCA skin®

dry skin relief bar

salicylic acid psoriasis and
seborrheic dermatitis cleanser

01 | cleanse

3.2 oz (90 g)